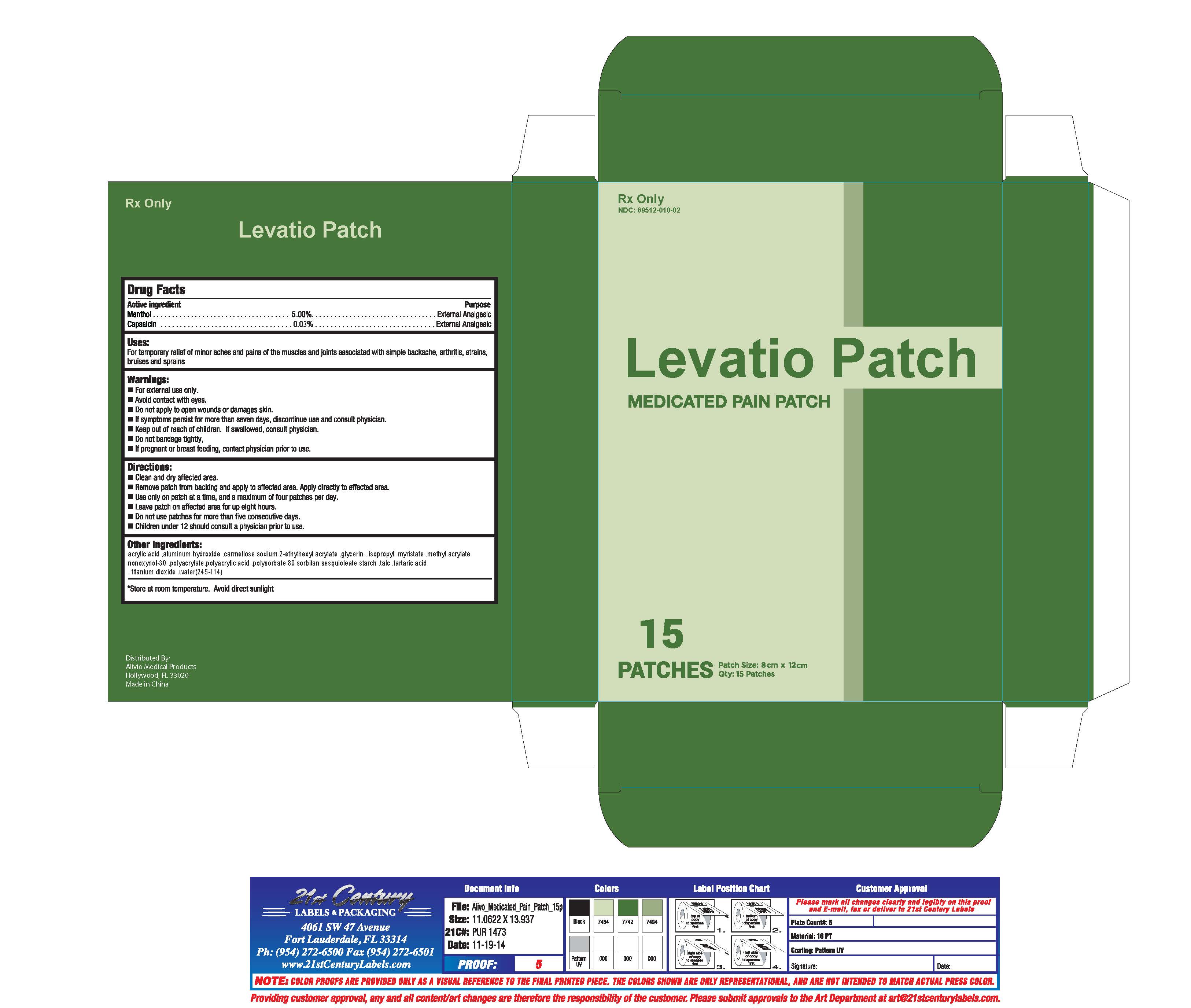 DRUG LABEL: Levatio Patch
NDC: 69512-010 | Form: PATCH
Manufacturer: Alivio Medical Products, LLC
Category: prescription | Type: HUMAN PRESCRIPTION DRUG LABEL
Date: 20150302

ACTIVE INGREDIENTS: MENTHOL 5 g/100 g; CAPSAICIN .03 g/100 g
INACTIVE INGREDIENTS: ACRYLIC ACID; ALUMINUM HYDROXIDE; CROSCARMELLOSE SODIUM; 2-ETHYLHEXYL ACRYLATE; GLYCERIN; ISOPROPYL MYRISTATE; METHYL ACRYLATE; NONOXYNOL-30; POLYACRYLAMIDE (10000 MW); POLYACRYLIC ACID (250000 MW); POLYSORBATE 80; TALC; TARTARIC ACID; TITANIUM DIOXIDE; WATER

Drug Facts

Active Ingredient

Menthol 5.00 %

Capsaicin 0.03 %

INACTIVE INGREDIENT

Other Ingredients:

acrylic acid ,aluminum hydroxide . carmellose sodium 2-ethylexyl acrylate glycerin . isopropyl myristate .methyl acrylate

nonoxynol-30 .poluacrylate.polyacrylic acid .polysorbate 80 sorbitan sesquioleate strach .talc .tartaric acid

.titanium dioxide .water(254-114)

Purpose

External Analgesic

External Analgesic

Uses:

For temporary relief of minor aches and pains of the muscles and joints associated with simple backache, arthritis, strains,

bruises and sprains

Warnings:

- For external use only
- Avoid contact with eyes
- Do not apply to open wounds or damages skin
- If symptoms persist for more than seven days, discontinue use and consult physician
- Keep out of reach of children. If swallowed, consult physician.
- Do not bandage tightly
- If pregnant or breast feeding, contact physician prior to use

Directions:

- Clean and dry affected area
- Remove patch from backing and apply to affected area. Apply directly to affected area.
- Use only on patch at a time, and a maximum of four patches per day.
- Leave patch of affected area for up to eight hours.
- Do not use patches for more than five consecutive days
- Children under 12 should consult a physician prior to use.

STORAGE AND HANDLING

Store at room temperature. Avoid direct sunlight.

PATIENT INFORMATION

Leveatio - menthol and capsaicin patch

Levatio Patch

Description

Levatio Patch contains capsaicin and menthol in a

localized topical dermal delivery system. The

capsaicin in Levatio is a synthetic equivalent of the

naturally occurring compound found in chili

peppers. Capsaicin is soluble in alcohol, acetone,

and ethyl acetate and very slightly soluble in water.

The menthol is slightly soluble in water.

Levatio is a single-use patch stored in a foil pouch.

Each Levatio patch is 8 cm x 12 cm and consists

of a polyester backing film coated with a

drug-containing silicone adhesive formulation,

and covered with a removable polyester release liner.

The empirical formula for capsaicin is C18H27NO31

with a molecular weight of 305.42. The chemical compound capsaicin

[(E)-8-methyl-N-vanillyl-6-nonenamide] is an

activating ligand for transient receptor

potential vanolloid 1 receptor (TRPV1)

The empirical formula for menthol is C10H20)1 with a

molecular weight of 156.27. The chemical compound menthol

[(1R,2S,5R)-2-isopropyl-5-methylcyclohexanol] is an activating

ligand for transient receptor potential cation channel subfamily M member 8 (TRPM8).

Each Levatio Patch contains 0.03% capsaicin (0,03

grams of capsaicin per patch) and 5% menthol (5 grams of menthol per patch). The Levatio Patch

contains the following inactive ingredients: acrylic acid, aluminum hydroxide, carmellose sodium

2-ethylexyl acrylate, glycerin, isopropyl myristate,

methyl acrylatenonoxynol-30, polyacrylate, polyacrylic acid, polysorbate 80 sorbitan

sesquioleate starch, talc, tartaric acid, titanium dioxide, water (245-114).

INDICATIONS AND USAGE

Levatio Patch is indicated for the temporary relief of minor aches and muscle pains

associated with arthritis, simple backache, strains, muscle soreness and stiffness.

Levatio Patch is an external analgesic/countrerirritant.

CONTRAINDICATIONS

Levatio Patch is indicated for those patients with a history of hypersensitivity

to any of the components of the preparation.

WARNINGS

*FOR EXTERNAL USE ONLY

*USE ONLY AS DIRECTED

*AVOID CONTACT WITH EYES AND MUCOUS MEMBRANES,

*DO NOT COVER WITH BANDAGE

*DO NOT USE ON WOUNDS OR DAMAGED SKIN.

*CONSULT PHYSICIAN FOR CHILDREN UNDER 12

DO NOT USE IF YOU ARE ALLERGIC TO MENTHOL.

*STOP USE AND ASK A DOCTOR IF SYMPTOMS PERSIST FOR MORE THAN

7 DAYS OR CLEAR UP AND OCCUR AGAIN WITHIN A FEW DAYS OR RASH,

ITCHING OR EXCESSIVE SKIN IRRITATION OCCURS.

*KEEP OUT OF REACH OF CHILDREN.

DOSAGE AND ADMINISTRATION

Levatio Patch contains 0.03% capsaicin and 5.00% menthol. Instructions for use

*Clean and dry affected area

*Cut open pouch and remove pouch

*Remove protective film and apply directly to area of pain

*Apply to affected area not more than 3 times daily

*Wash hands with soap after applying patch

*Reseal pouch containing unused patches

DIRECTIONS

Adults and children 12 years and over - apply to affected area change patch 1 to 2 times daily

Children under 12 years - Consult physician before use

HOW SUPPLIED

Levatio Patch is supplied in 3 re-sealable pouches each containing 5 patches. NDC 69512-010-02

15 Patches per carton

Storage: Store at 20 to 25 C (68 to 77 F)

Avoid direct sunlight

Distributed by: Alivio Medical Products, LLC

Hollywood, FL